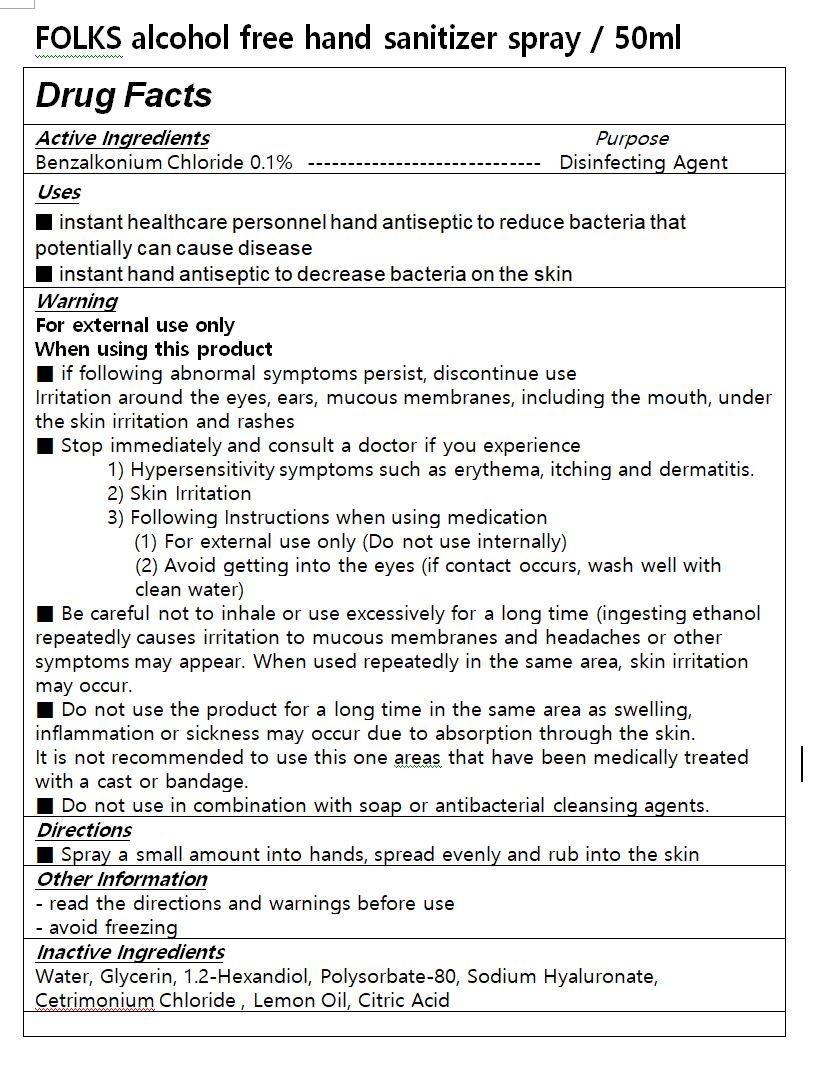 DRUG LABEL: FOLKS alcohol free hand sanitizer
NDC: 74538-0007 | Form: SPRAY
Manufacturer: WORLDCHEM CO LTD
Category: otc | Type: HUMAN OTC DRUG LABEL
Date: 20200530

ACTIVE INGREDIENTS: BENZALKONIUM CHLORIDE 0.1 g/100 mL
INACTIVE INGREDIENTS: WATER; LEVOMENTHOL; GLYCERIN; CETRIMONIUM CHLORIDE; 1,2-HEXANEDIOL; POLYSORBATE 80; HYALURONATE SODIUM

ACTIVE INGREDIENT

Benzalkonium Chloride 0.1%

INACTIVE INGREDIENT

Water, Glycerin, 1.2-Hexandiol, Polysorbate-80, Sodium Hyaluronate, Cetrimonium Chloride , Lemon Oil, Citric Acid

PURPOSE

■ instant healthcare personnel hand antiseptic to reduce bacteria that potentially can cause disease

■ instant hand antiseptic to decrease bacteria on the skin

WARNINGS

■ if following abnormal symptoms persist, discontinue use

Irritation around the eyes, ears, mucous membranes, including the mouth, under the skin irritation and rashes

■ Stop immediately and consult a doctor if you experience

1) Hypersensitivity symptoms such as erythema, itching and dermatitis.

2) Skin Irritation

3) Following Instructions when using medication

(1) For external use only (Do not use internally)

(2) Avoid getting into the eyes (if contact occurs, wash well with clean water)

■ Be careful not to inhale or use excessively for a long time (ingesting ethanol repeatedly causes irritation to mucous membranes and headaches or other symptoms may appear. When used repeatedly in the same area, skin irritation may occur.

■ Do not use the product for a long time in the same area as swelling, inflammation or sickness may occur due to absorption through the skin.

It is not recommended to use this one areas that have been medically treated with a cast or bandage.

■ Do not use in combination with soap or antibacterial cleansing agents.

• Keep Out of Reach of Children.

INDICATIONS AND USAGE

■ spray a small amount into hands, spread evenly and rub into the skin

DOSAGE AND ADMINISTRATION

for topical use only